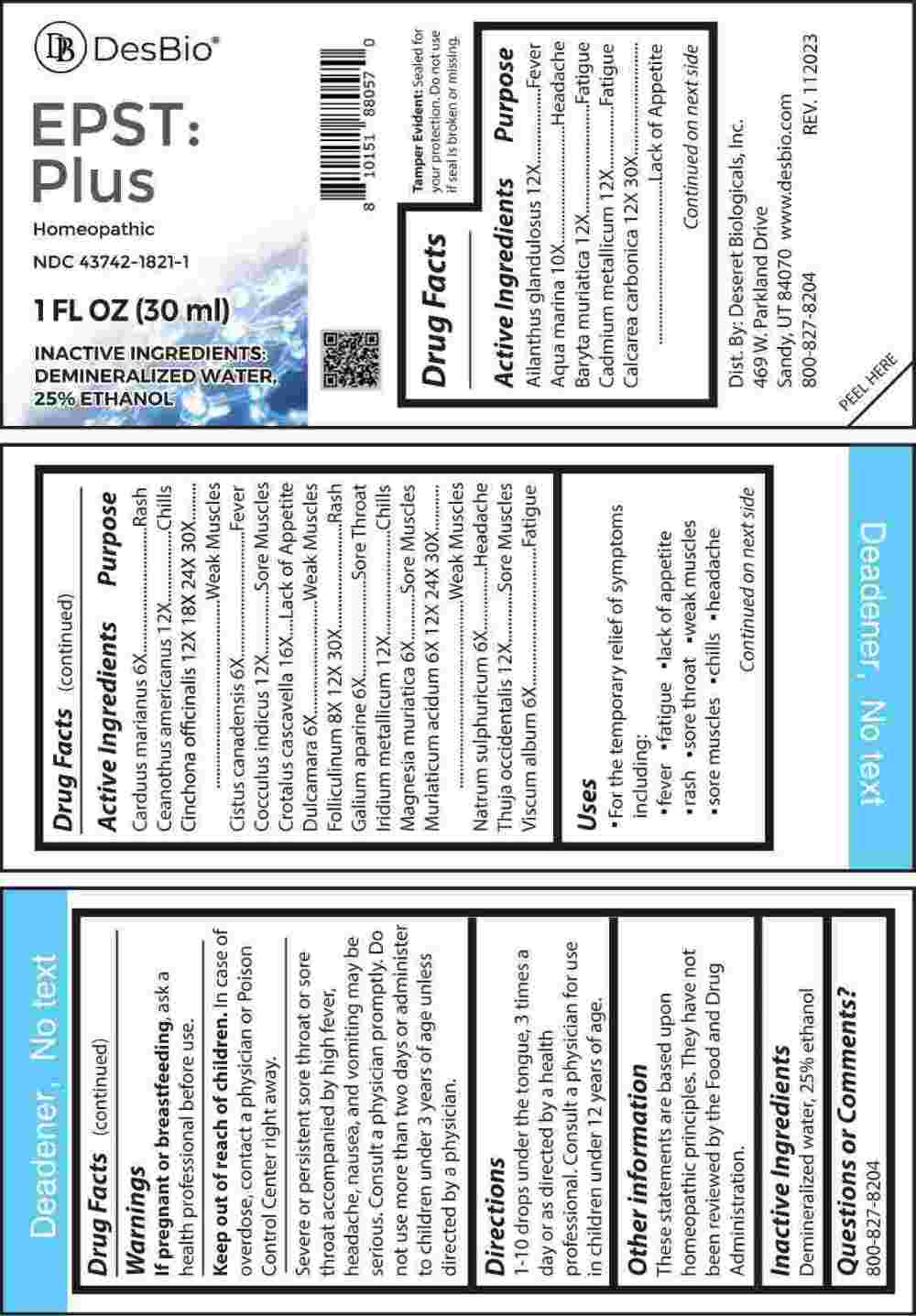 DRUG LABEL: EPST PLUS
NDC: 43742-1821 | Form: LIQUID
Manufacturer: Deseret Biologicals, Inc.
Category: homeopathic | Type: HUMAN OTC DRUG LABEL
Date: 20240227

ACTIVE INGREDIENTS: MILK THISTLE 6 [hp_X]/1 mL; HELIANTHEMUM CANADENSE 6 [hp_X]/1 mL; SOLANUM DULCAMARA TOP 6 [hp_X]/1 mL; GALIUM APARINE WHOLE 6 [hp_X]/1 mL; MAGNESIUM CHLORIDE 6 [hp_X]/1 mL; SODIUM SULFATE 6 [hp_X]/1 mL; VISCUM ALBUM FRUITING TOP 6 [hp_X]/1 mL; HYDROCHLORIC ACID 6 [hp_X]/1 mL; ESTRONE 8 [hp_X]/1 mL; SODIUM CHLORIDE 10 [hp_X]/1 mL; AILANTHUS ALTISSIMA FLOWERING TWIG 12 [hp_X]/1 mL; BARIUM CHLORIDE DIHYDRATE 12 [hp_X]/1 mL; CADMIUM 12 [hp_X]/1 mL; CEANOTHUS AMERICANUS LEAF 12 [hp_X]/1 mL; ANAMIRTA COCCULUS SEED 12 [hp_X]/1 mL; IRIDIUM 12 [hp_X]/1 mL; THUJA OCCIDENTALIS LEAFY TWIG 12 [hp_X]/1 mL; CINCHONA OFFICINALIS BARK 12 [hp_X]/1 mL; OYSTER SHELL CALCIUM CARBONATE, CRUDE 12 [hp_X]/1 mL; CROTALUS DURISSUS TERRIFICUS VENOM 16 [hp_X]/1 mL
INACTIVE INGREDIENTS: WATER; ALCOHOL

DRUG FACTS:

ACTIVE INGREDIENTS:

Ailanthus Glandulosus 12X, Aqua Marina 10X, Baryta Muriatica 12X, Cadmium Metallicum 12X, Calcarea Carbonica 12X, 30X, Carduus Marianus 6X, Ceanothus Americanus 12X, Cinchona Officinalis 12X, 18X, 24X, 30X, Cistus Canadensis 6X, Cocculus Indicus 12X, Crotalus Cascavella 16X, Dulcamara 6X, Folliculinum 8X, 12X, 30X, Galium Aparine 6X, Iridium Metallicum 12X, Magnesia Muriatica 6X, Muriaticum Acidum 6X, 12X, 24X, 30X, Natrum Sulphuricum 6X, Thuja Occidentalis 12X, Viscum Album 6X.

PURPOSE:

Ailanthus Glandulosus - Fever, Aqua Marina - Headache, Baryta Muriatica - Fatigue, Cadmium Metallicum - Fatigue, Calcarea Carbonica – Lack of Appetite, Carduus Marianus - Rash, Ceanothus Americanus - Chills, Cinchona Officinalis – Weak Muscles, Cistus Canadensis - Fever, Cocculus Indicus – Sore Muscles, Crotalus Cascavella – Lack of Appetite, Dulcamara – Weak Muscles, Folliculinum - Rash, Galium Aparine – Sore Throat, Iridium Metallicum - Chills, Magnesia Muriatica – Sore Muscles, Muriaticum Acidum – Weak Muscles, Natrum Sulphuricum - Headache, Thuja Occidentalis – Sore Muscles, Viscum Album - Fatigue

USES:

• For the temporary relief of symptoms including:

• fever • fatigue • lack of appetite • rash

• sore throat • weakness muscles

• sore muscles • chills • headaches.

These statements are based upon homeopathic principles. They have not been reviewed by the Food and Drug Administration.

WARNINGS:

If pregnant or breastfeeding, ask a health professional before use.

Keep out of reach of children. In case of overdose, contact a physician or Poison Control Center right away.

Severe or persistent sore throat or sore throat accompanied by high fever, headache, nausea, and vomiting may be serious. Consult a physician promptly. Do not use more than two days or administer to children under 3 years of age unless directed by a physician.

Tamper Evident: Sealed for your protection. Do not use if seal is broken or missing.

KEEP OUT OF REACH OF CHILDREN:

In case of overdose, contact a physician or Poison Control Center right away.

DIRECTIONS:

1-10 drops under the tongue, 3 times a day or as directed by a health professional. Consult a physician for use in children under 12 years of age.

INACTIVE INGREDIENTS:

Demineralized water, 25% ethanol

QUESTIONS:

Dist. By: Deseret Biologicals, Inc.

469 W. Parkland Drive

Sandy, UT 84070

www.desbio.com

800-827-8204

PACKAGE LABEL DISPLAY:

Des Bio

EPST:Plus

Homeopathic
NDC 43742-1821-1

1 FL OZ (30 ml)